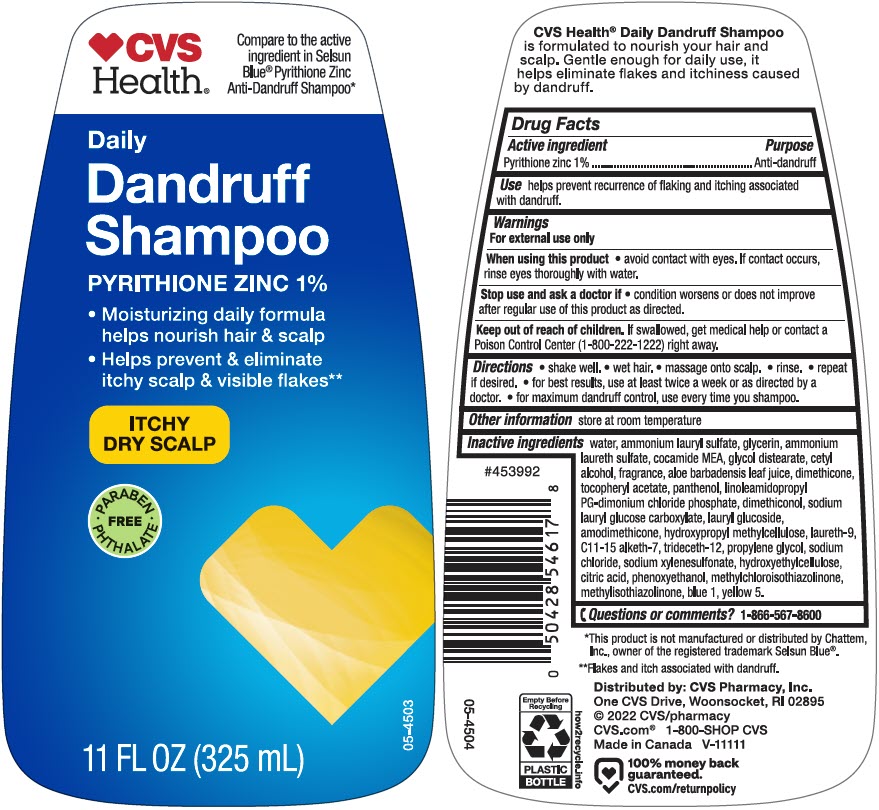 DRUG LABEL: CVS Daily Dandruff
NDC: 51316-178 | Form: SHAMPOO
Manufacturer: CVS Health
Category: otc | Type: HUMAN OTC DRUG LABEL
Date: 20240927

ACTIVE INGREDIENTS: Pyrithione Zinc 10 mg/1 mL
INACTIVE INGREDIENTS: Water; Ammonium Lauryl Sulfate; Glycerin; AMMONIUM LAURETH-5 SULFATE; COCO MONOETHANOLAMIDE; Glycol Distearate; Cetyl Alcohol; ALOE VERA LEAF; Dimethicone; .ALPHA.-TOCOPHEROL ACETATE, DL-; Panthenol; LINOLEAMIDOPROPYL PROPYLENE GLYCOL-DIMONIUM CHLORIDE PHOSPHATE; DIMETHICONOL (2000 CST); Lauryl Glucoside; AMODIMETHICONE (800 CST); HYPROMELLOSE, UNSPECIFIED; POLIDOCANOL; C11-15 Alketh-7; Trideceth-12; Propylene Glycol; Sodium Chloride; Sodium Xylenesulfonate; HYDROXYETHYL CELLULOSE, UNSPECIFIED; CITRIC ACID MONOHYDRATE; Phenoxyethanol; Methylisothiazolinone; FD&C BLUE NO. 1; FD&C YELLOW NO. 5

CVS Daily Dandruff Shampoo
Anti-dandruff

Drug Facts

Active ingredient

Pyrithione Zinc 1%

Purpose

Anti-dandruff

Use

helps prevent recurrence of flaking and itching associated with dandruff.

Warnings

For external use only.

When using this product

- avoid contact with the eyes. If contact occurs, rinse eyes thoroughly with water.

Stop use and ask a doctor if

- condition worsens or does not improve after regular use of this product as directed.

Keep out of reach of children. If swallowed, get medical help or contact a Poison Control Center (1-800-222-1222) right away.

Directions

- shake well.
- wet hair.
- massage onto scalp.
- rinse.
- repeat if desired.
- for best results, use at least twice a week or as directed by a doctor.
- for maximum dandruff control, use every time you shampoo.

Other information

- store at room temperature

Inactive ingredients

water, ammonium lauryl sulfate, glycerin, ammonium laureth sulfate, cocamide MEA, glycol distearate, cetyl alcohol, fragrance, aloe barbadensis leaf juice, dimethicone, tocopheryl acetate, panthenol, linoleamidopropyl PG dimonium chloride phosphate, dimethiconol, sodium lauryl glucose carboxylate, lauryl glucoside, amodimethicone, hydroxypropyl methylcellulose, laureth-9, c11-15 alketh-7, trideceth-12, propylene glycol, sodium chloride, sodium xylenesulfonate, hydroxyethylcellulose, citric acid, phenoxyethanol, methylisothiazolinone, blue 1, yellow 5.

Questions or comments?

1-866-567-8600

Distributed by: CVS Pharmacy, Inc.
One CVS Drive, Woonsocket, RI 02895

PRINCIPAL DISPLAY PANEL - 325 mL Bottle Label

CVS
Health®

Compare to the active
ingredient in Selsun
Blue® Pyrithione Zinc
Anti-Dandruff Shampoo*

Daily
Dandruff
Shampoo

PYRITHIONE ZINC 1%

- Moisturizing daily formula
  helps nourish hair & scalp
- Helps prevent & eliminate
  itchy scalp & visible flakes**

ITCHY
DRY SCALP

• PARABEN
PHTHALATE •
FREE

05-4503

11 FL OZ (325 mL)